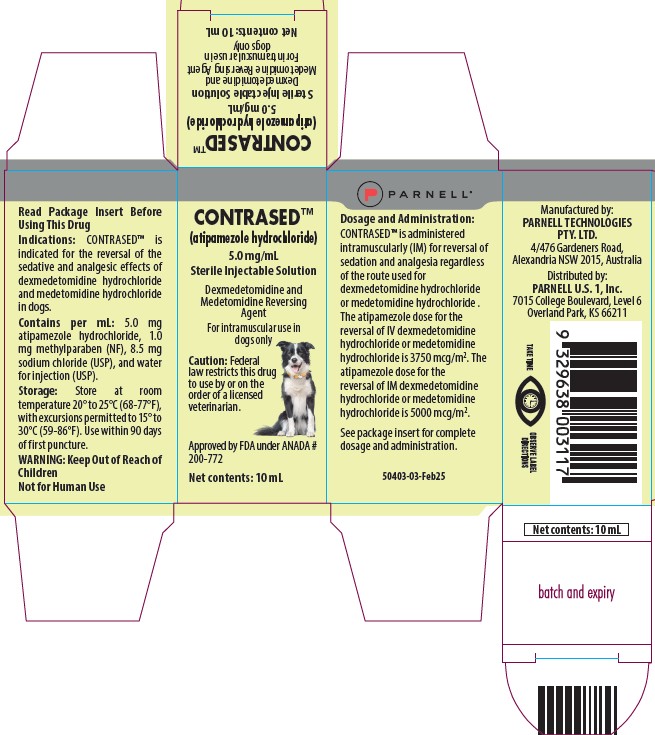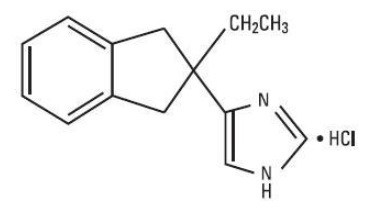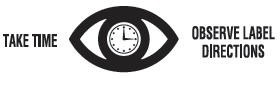 DRUG LABEL: CONTRASED
NDC: 68504-007 | Form: INJECTION, SOLUTION
Manufacturer: Parnell Technologies Pty Ltd
Category: animal | Type: PRESCRIPTION ANIMAL DRUG LABEL
Date: 20251105

ACTIVE INGREDIENTS: ATIPAMEZOLE HYDROCHLORIDE 5 mg/1 mL
INACTIVE INGREDIENTS: SODIUM CHLORIDE 8.5 mg/1 mL

CONTRASED™
(atipamezole hydrochloride)
5.0 mg/mL
Sterile Injectable Solution
Dexmedetomidine and Medetomidine Reversing Agent

For intramuscular use in dogs only

CAUTION

Federal law restricts this drug to use by or on the order of a licensed veterinarian.

DESCRIPTION

CONTRASED™ (atipamezole hydrochloride) is a synthetic α2-adrenergic antagonist. The chemical name is 4-(2-ethyl-2,3-dihydro-1H-inden-2-yl)-1H-imidazole hydrochloride. The molecular formula is C14H16N2 • HCl and structural formula is:

Each mL of CONTRASED™ contains 5.0 mg atipamezole hydrochloride, 1.0 mg methylparaben (NF), 8.5 mg sodium chloride (USP), and water for injection (USP).

INDICATIONS

CONTRASED™ is indicated for the reversal of the sedative and analgesic effects of dexmedetomidine hydrochloride, and medetomidine hydrochloride in dogs.

DOSAGE AND ADMINISTRATION

CONTRASED™ is administered intramuscularly (IM) for reversal of sedation and analgesia regardless of the route used for dexmedetomidine hydrochloride or medetomidine hydrochloride. The atipamezole dose for the reversal of IV dexmedetomidine hydrochloride or medetomidine hydrochloride is 3750 mcg/m^2. The atipamezole dose for the reversal of IM dexmedetomidine hydrochloride or medetomidine hydrochloride is 5000 mcg/m^2.

The dosage of CONTRASED™ is calculated based on body surface area. Use the following tables to determine the correct injection volume or the correct CONTRASED™ dosage on the basis of kilograms of body weight.

Note that the mcg/kg dosage decreases as body weight increases.

Table 1: Atipamezole dosing for reversal of IV dexmedetomidine hydrochloride- or medetomidine hydrochloride-induced sedation/analgesia:

Dose table for CONTRASED™ (3750 mcg/m^2) when dexmedetomidine hydrochloride or medetomidine hydrochloride is given IV
For # lb | For # kg | dose = mcg/kg | Volume = mL CONTRASED™
4-7 | 2-3 | 300 | 0.1
7-9 | 3-4 | 250 | 0.15
9-11 | 4-5 | 230 | 0.2
11-22 | 5-10 | 200 | 0.3
22-33 | 10-15 | 170 | 0.4
33-44 | 15-20 | 150 | 0.5
44-55 | 20-25 | 140 | 0.6
55-66 | 25-30 | 130 | 0.7
66-81 | 30-37 | 120 | 0.8
81-99 | 37-45 | 110 | 0.9
99-110 | 45-50 | 105 | 1.0
110-132 | 50-60 | 100 | 1.1
132-143 | 60-65 | 95 | 1.2
143-165 | 65-75 | 93 | 1.3
165-176 | 75-80 | 91 | 1.4
>176 | >80 | 90 | 1.5

Table 2: Atipamezole dosing for reversal of IM dexmedetomidine hydrochloride- or medetomidine hydrochloride- induced sedation/analgesia:

Dose table for CONTRASED™ (5000 mcg/m^2) when dexmedetomidine hydrochloride or medetomidine hydrochloride is given IM
For # lb | For # kg | dose = mcg/kg | volume = mL CONTRASED™
4-7 | 2-3 | 400 | 0.15
7-9 | 3-4 | 350 | 0.2
9-11 | 4-5 | 300 | 0.3
11-22 | 5-10 | 250 | 0.4
22-29 | 10-13 | 230 | 0.5
29-33 | 13-15 | 210 | 0.6
33-44 | 15-20 | 200 | 0.7
44-55 | 20-25 | 180 | 0.8
55-66 | 25-30 | 170 | 0.9
66-73 | 30-33 | 160 | 1.0
73-81 | 33-37 | 150 | 1.1
81-99 | 37-45 | 145 | 1.2
99-110 | 45-50 | 140 | 1.3
110-121 | 50-55 | 135 | 1.4
121-132 | 55-60 | 130 | 1.5
132-143 | 60-65 | 128 | 1.6
143-154 | 65-70 | 125 | 1.7
154-176 | 70-80 | 123 | 1.8
>176 | >80 | 120 | 1.9

CONTRAINDICATIONS

Since atipamezole is always used concomitantly with dexmedetomidine or medetomidine, it should not be used in dogs with the following conditions: cardiac disease, respiratory disorders, liver or kidney diseases, dogs in shock, severely debilitated dogs, or dogs stressed due to extreme heat, cold or fatigue.
Administration of atipamezole is contraindicated in dogs with a known hypersensitivity to the drug.

HUMAN WARNINGS

Not for human use. Keep out of reach of children.

Atipamezole hydrochloride can be absorbed and may cause irritation following direct exposure to skin, eyes, or mouth. In case of accidental eye exposure, flush with water for 15 minutes. In case of accidental skin exposure, wash with soap and water. Remove contaminated clothing. If irritation or other adverse reaction occurs (for example, increased heart rate, tremor, muscle cramps), seek medical attention.

In case of accidental oral exposure or injection, seek medical attention. Caution should be used while handling and using filled syringes.

Users with cardiovascular disease (for example, hypertension or ischemic heart disease) should take special precautions to avoid any exposure to this product.

The safety data sheet (SDS) contains more detailed occupational safety information.

To report adverse reactions in users or to obtain a copy of the SDS for this product call 1 800 887 2763.

Note to Physician: This product contains an alpha2-adrenergic antagonist.

PRECAUTIONS

1. Handling: Atipamezole hydrochloride can produce an abrupt reversal of sedation; therefore, dogs that have recently received atipamezole hydrochloride should be handled with caution. The potential for apprehensive or aggressive behavior should be considered in the handling of dogs emerging from sedation, especially in dogs predisposed to nervousness or fright. Also, avoid situations where a dog might fall.

2. Sedation relapse: While atipamezole does reverse the clinical signs associated with medetomidine or dexmedetomidine sedation, complete physiologic return to pretreatment status may not be immediate or may be temporary, and dogs should be monitored for sedation relapse. Sedation relapse is more likely to occur in dogs that receive an alpha2-agonist by the IV route, compared to dogs that are sedated using the IM route. Animals should be monitored closely for persistent hypothermia, bradycardia, and depressed respiration, until signs of recovery persist.

3. Analgesia reversal: Atipamezole reverses analgesic effects as well as sedative effects. Additional procedures for the control of pain may be required.

4. Debilitated dogs: The safety of atipamezole has not been evaluated in dogs with compromised health. Geriatric, debilitated, and ill dogs are more likely to experience adverse reactions associated with the administration of alpha2-antagonists (as well as alpha2-agonists). Dogs with abnormalities associated with the cardiovascular system are especially at risk.

5. Breeding dogs: Atipamezole hydrochloride has not been evaluated in breeding dogs; therefore, the drug is not recommended for use in pregnant or lactating dogs, or in dogs intended for breeding.

6. Minimum age and weight: Atipamezole hydrochloride has not been evaluated in dogs less than four months of age or in dogs weighing less than 4.4 lbs (2 kg).

ADVERSE REACTIONS

Occasional vomiting may occur. At times, a period of excitement or apprehensiveness may be seen in dogs treated with atipamezole. Other effects of atipamezole include hypersalivation, diarrhea, and tremors.

Contact Information: To report suspected adverse drug events, for technical assistance or to obtain a copy of the Safety Data Sheet, contact Parnell at 1-800-887-2763. For additional information about adverse drug experience reporting for animal drugs, contact FDA at 1-888-FDA-VETS or http://www.fda.gov/reportanimalae.

CLINICAL PHARMACOLOGY

Atipamezole is a potent alpha2-antagonist which selectively and competitively inhibits alpha2-adrenergic receptors. The result of atipamezole administration in the dog is the rapid recovery from the sedative and analgesic effects produced by the alpha2-adrenergic agonists dexmedetomidine or medetomidine. Atipamezole does not reverse the effects of other classes of sedatives, anesthetics, or analgesics.

Atipamezole is rapidly absorbed following intramuscular injection; maximum serum concentration is reached in approximately 10 minutes. Onset of arousal is usually apparent within 5 to 10 minutes of injection, depending on the depth and duration of dexmedetomidine- or medetomidine-induced sedation. Elimination half-life from serum is less than 3 hours. Atipamezole undergoes extensive hepatic biotransformation, with excretion of metabolites primarily in urine.

Dexmedetomidine or medetomidine activation of peripheral and central alpha2-adrenergic receptors induces a pattern of pharmacological responses that include sedation, reduction of anxiety, analgesia, and bradycardia.

Blood pressure is initially increased due to peripheral vasoconstriction and thereafter drops to normal or slightly below normal levels.

A transient, decrease in systolic blood pressure occurs immediately after administration of atipamezole to dexmedetomidine- or medetomidine-sedated dogs, followed by a transient increase in arterial pressure within 10 minutes compared to pre-atipamezole levels. This is the opposite of the response to alpha2-agonist treatment, and is probably due to atipamezole-induced peripheral vasodilation.

Atipamezole administration rapidly abolishes dexmedetomidine- or medetomidine- induced bradycardia, usually within 3 minutes. The magnitude of the effect of atipamezole on heart rate is greater when dexmedetomidine is administered intravenously compared to intramuscularly. Dogs receiving medetomidine or IM dexmedetomidine may not return to pre-sedative heart rates after atipamezole administration and some dogs briefly show heart rate elevations above baseline. Respiratory rate increases following atipamezole injection.

EFFECTIVENESS

One hundred and nine dogs received atipamezole in the field study (55 dogs received the reversal agent following dexmedetomidine; 54 following medetomidine). The mean age was 5.9 years and ranged between 17 weeks and 16 years. The mean weight was 45.5 lbs (20.7 kg), ranging from 4.8 lbs to 117 lbs (2.2 kg to 53.2 kg). Atipamezole was administered by the IM route of administration, within a range of 39-57 minutes after administration of either dexmedetomidine (IV and IM) or medetomidine (IV and IM).

Atipamezole reversed the effects of dexmedetomidine and medetomidine in all cases. In dexmedetomidine treated dogs, the onset of reversal was evident within 5 minutes after administration of atipamezole (57% could stand). Within 15 minutes, 96% of dexmedetomidine treated dogs were standing, 92% responded normally to sound, 86% had a normal muscle tone of jaw, and >90% had a normal pedal reflex response.

Responses in dogs treated with medetomidine were similar or slightly later.

Following atipamezole, heart rate increased between 0 and 5 minutes following either alpha2-agonist (IV dexmedetomidine dogs had heart rates from 60 to 85 bpm, and IV medetomidine dogs from 51 to 67 bpm; IM dexmedetomidine dogs had heart rates from 45 to 73 bpm, and IM medetomidine dogs from 52 to 79 bpm). Bradycardia resolved more slowly in the IM treatment groups. The body temperature remained at the same level during the 120 minutes of follow-up after atipamezole administration. Respiratory rates increased toward normal between 0 and 5 minutes after the administration of atipamezole in all treatment groups. Mucous membranes were described as normal after 5 minutes in 91% of dexmedetomidine dogs (IV or IM). By 120 minutes, 96% were normal (after IV dexmedetomidine) or 100% were normal (after IM dexmedetomidine).

Many physiological responses were slightly slower to return toward normal when dogs were treated with medetomidine IV or IM.

No adverse events were reported in the atipamezole treated dogs.

ANIMAL SAFETY

Atipamezole was tolerated in healthy dogs receiving 10X the recommended dose and in dogs receiving repeated doses at 1, 3, and 5X the recommended dose, in the absence of an alpha2-agonist. Signs were dose-related and included excitement, panting, trembling, vomiting, soft or liquid feces and scleral injection. At 10X the recommended dose, increases in creatine kinase, AST, and ALT were noted. Creatine kinase also increased in 3 (of 6) dogs in the 3X treatment group. Localized skeletal muscle injury was seen at the injection site but no associated clinical signs or complications were observed. Dogs receiving the recommended atipamezole dose in the absence of medetomidine or dexmedetomidine exhibited no adverse clinical signs. In additional safety studies, adverse events were absent up to the 3X dose of atipamezole when its administration followed medetomidine or dexmedetomidine sedation.

In a separate safety study using a crossover design, 5 dogs received atipamezole after dexmedetomidine (IV and IM). Dexmedetomidine’s effects on blood pressure, heart rate, respiratory rate, and cardiac conduction times were reversed by atipamezole. However, heart rate and cardiac conduction times did not return to predexmedetomidine values.

Heart rate increases after atipamezole were closer to baseline values in dogs treated with dexmedetomidine IV (compared to IM).

STORAGE INFORMATION

Store at room temperature 20° to 25°C (68-77°F), with excursions permitted to 15° to 30°C (59-86°F). Use within 90 days of first puncture.

HOW SUPPLIED

CONTRASED™ is supplied in 10-mL, multidose vials containing 5.0 mg of atipamezole hydrochloride per mL.

Approved by FDA under ANADA # 200-772

Manufactured by:
PARNELL TECHNOLOGIES PTY. LTD.
4/476 Gardeners Road
Alexandria NSW 2015 Australia

Distributed by:
PARNELL U.S. 1, Inc.
7015 College Boulevard, Level 6,
Overland Park, KS, 66211

10 mL: 50457-01-July24

PACKAGE LABEL

PARNELL®

CONTRASED™

(atipamezole hydrochloride)

5.0 mg/mL

Sterile Injectable Solution

Dexmedetomidine and Medetomidine Reversing Agent

For intramuscular use in dogs only

Caution: Federal law restricts this drug to use by or on the order of a licensed veterinarian.

Approved by FDA under ANADA # 200-772

Net Contents: 10 mL